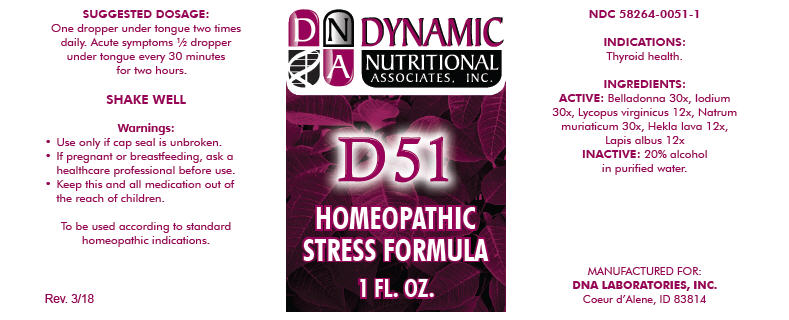 DRUG LABEL: D-51
NDC: 58264-0051 | Form: SOLUTION
Manufacturer: DNA Labs, Inc.
Category: homeopathic | Type: HUMAN OTC DRUG LABEL
Date: 20250113

ACTIVE INGREDIENTS: ATROPA BELLADONNA 30 [hp_X]/1 mL; IODINE 30 [hp_X]/1 mL; LYCOPUS VIRGINICUS 12 [hp_X]/1 mL; SODIUM CHLORIDE 30 [hp_X]/1 mL; HEKLA LAVA 12 [hp_X]/1 mL; CALCIUM HEXAFLUOROSILICATE 12 [hp_X]/1 mL
INACTIVE INGREDIENTS: ALCOHOL; WATER

D-51

NDC 58264-0051-1

INDICATIONS

PURPOSE

Thyroid health.

INGREDIENTS

ACTIVE

Belladonna 30x, Iodium 30x, Lycopus virginicus 12x, Natrum muriaticum 30x, Hekla lava 12x, Lapis albus 12x

INACTIVE

20% alcohol in purified water.

SUGGESTED DOSAGE

One dropper under tongue two times daily. Acute symptoms ½ dropper under tongue every 30 minutes for two hours.

STORAGE AND HANDLING

SHAKE WELL

Warnings

- Use only if cap seal is unbroken.

PREGNANCY OR BREAST FEEDING

- If pregnant or breastfeeding, ask a healthcare professional before use.

KEEP OUT OF REACH OF CHILDREN

- Keep this and all medication out of the reach of children.

To be used according to standard homeopathic indications.

PRINCIPAL DISPLAY PANEL - 1 FL. OZ. Bottle Label

DYNAMIC
NUTRITIONAL
ASSOCIATES, INC.

D 51

HOMEOPATHIC
STRESS FORMULA

1 FL. OZ.